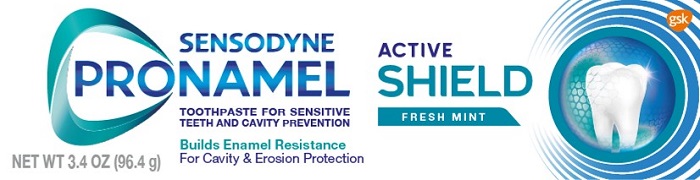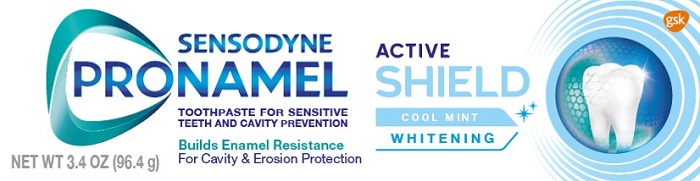 DRUG LABEL: SENSODYNE PRONAMEL

NDC: 0135-0700 | Form: PASTE
Manufacturer: Haleon US Holdings LLC
Category: otc | Type: HUMAN OTC DRUG LABEL
Date: 20240304

ACTIVE INGREDIENTS: POTASSIUM NITRATE 50 mg/1 g; SODIUM FLUORIDE 1.15 mg/1 g
INACTIVE INGREDIENTS: WATER; SORBITOL; HYDRATED SILICA; GLYCERIN; POLYETHYLENE GLYCOL 400; SODIUM LACTATE; XANTHAN GUM; COCAMIDOPROPYL BETAINE; SODIUM METHYL COCOYL TAURATE; TITANIUM DIOXIDE; SACCHARIN SODIUM; SODIUM HYDROXIDE

Drug Facts

Active ingredient

Potassium nitrate 5%

Sodium fluoride 0.25% (0.15% w/v fluoride ion)

Purposes

Antihypersensitivity

Anticavity

Uses

- builds increasing protection against painful sensitivity of the teeth to cold, heat, acids, sweets, or contact.
- aids in the prevention of dental cavities.

Warnings

Stop use and ask a dentist if

- the problem persists or worsens. Sensitive teeth may indicate a serious problem that may need prompt care by a dentist.
- pain/sensitivity still persists after 4 weeks of use.

Keep out of reach of children.

If more than used for brushing is accidentally swallowed, get medical help or contact a Poison Control Center right away.

Directions

- adults and children 12 years of age and older:
  - apply at least a 1-inch strip of the product onto a soft bristle toothbrush.
  - brush teeth thoroughly for at least 1 minute twice a day (morning and evening), and not more than 3 times a day, or as recommended by a dentist or doctor. Make sure to brush all sensitive areas of the teeth. Minimize swallowing. Spit out after brushing.
- children under 12 years of age:Consult a dentist or doctor.

Other information

- do not store above 25°C (77°F)

Inactive ingredients

water, sorbitol, hydrated silica, glycerin, PEG-8, sodium lactate, flavor, xanthan gum, cocamidopropyl betaine, sodium methyl cocoyl taurate, titanium dioxide, sodium saccharin, PVM/MA copolymer, sodium hydroxide

Questions or comments?

1-866-844-2797

Additional information (Fresh Mint)

SENSODYNE PRONAMEL ACTIVE SHIELD

No 1 dentist recommended brand for enamel protection & strengthening.

Enamel is your natural defense shield for healthy teeth. Everyday it can be weakened by dietary or sugar acids which make your teeth more at risk to cavities and enamel wear.

New Pronamel Active Shield – start building resistance today to help keep your teeth strong and healthy for life.**

Acids from foods, drinks or sugars weaken the enamel surface

Pronamel has a proven formula that actively reinforces weakened enamel

Proven to actively reinforce weakened enamel

Developed for defense against cavities and enamel wear by remineralizing your weakened enamel. Pronamel Active Shield helps with:

2X stronger resistance against dietary acids from Day 1*

Helps shield the enamel against erosion and cavities

Enhanced foaming action# with extra fresh mint to leave the whole mouth feeling clean and fresh

*vs your mouth’s natural defenses

** With continued twice daily brushing, a healthy diet and regular dental visits.

#vs Pronamel Daily Protection

ALWAYS FOLLOW THE LABEL

Trademarks owned or licensed by GSK. ©2022 GSK or licensor.

Distributed by: GSK Consumer Healthcare,Warren, NJ 07059

Additional information (Cool Mint)

S ENSODYNE PRONAMEL ACTIVE SHIELD

No 1 dentist recommended brand for enamel protection & strengthening.

Enamel is your natural defense shield for healthy teeth. Everyday it can be weakened by dietary or sugar acids which make your teeth more at risk to cavities and enamel wear.

New Pronamel Active Shield – start building resistance today to help keep your teeth strong and healthy for life.**

Acids from foods, drinks or sugars weaken the enamel surface

Pronamel has a proven formula that actively reinforces weakened enamel

Proven to actively reinforce weakened enamel

Developed for defense against cavities and enamel wear by remineralizing your weakened enamel. Pronamel Active Shield helps with:

2X stronger resistance against dietary acids from Day 1*

Helps shield the enamel against erosion and cavities

Enhanced foaming action# with extra fresh mint to leave the whole mouth feeling clean and fresh

Effectively and gently removes stains for whiter teeth

*vs your mouth’s natural defenses

** With continued twice daily brushing, a healthy diet and regular dental visits.

#vs Pronamel Daily Protection

ALWAYS FOLLOW THE LABEL

Trademarks owned or licensed by GSK. ©2022 GSK or licensor.

Distributed by: GSK Consumer Healthcare,Warren, NJ 07059

Principal Display Panel

SENSODYNE

PRONAMEL ACTIVE SHIELD

TOOTHPASTE FOR SENSITIVE TEETH AND CAVITY PREVENTION

FRESH MINT

Builds Enamel Resistance

For Cavity & Erosion Protection

NET WT 3.4 OZ (96.4 g)

62000000200006 – Front Carton

Principal Display Panel

SENSODYNE

PRONAMEL

ACTIVE SHIELD

TOOTHPASTE FOR SENSITIVE TEETH AND CAVITY PREVENTION

COOL MINT WHITENING

Builds Enamel Resistance

For Cavity & Erosion Protection

NET WT 3.4 OZ (96.4 g)

620000000200004 – Front Carton